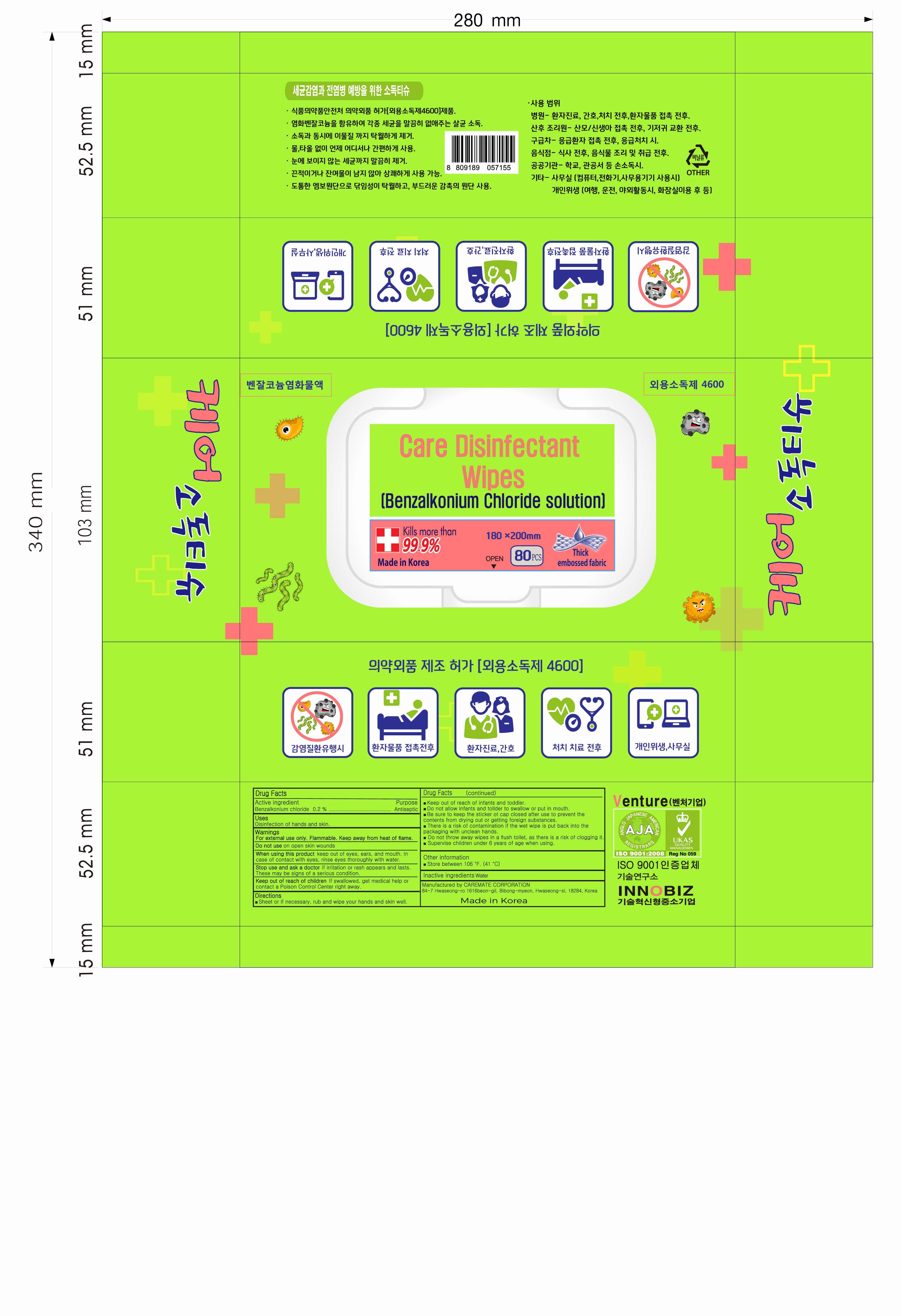 DRUG LABEL: Care Disinfectant Wipes
NDC: 78878-002 | Form: CLOTH
Manufacturer: CAREMATE CORPORATION
Category: otc | Type: HUMAN OTC DRUG LABEL
Date: 20200609

ACTIVE INGREDIENTS: BENZALKONIUM CHLORIDE 0.002 1/1 1
INACTIVE INGREDIENTS: WATER

Care Disinfectant Wipes | 80 WIPES in 1 packet | 78878-002-80